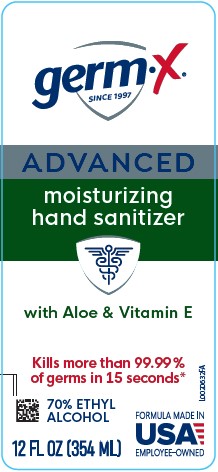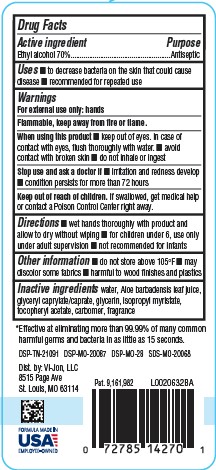 DRUG LABEL: Advanced Hand Sanitizer with Aloe
NDC: 83986-996 | Form: GEL
Manufacturer: UpLift Brands, LLC
Category: otc | Type: HUMAN OTC DRUG LABEL
Date: 20250926

ACTIVE INGREDIENTS: ALCOHOL 70 mL/100 mL
INACTIVE INGREDIENTS: WATER; ALOE VERA LEAF; GLYCERYL MONOCAPRYLOCAPRATE; GLYCERIN; ISOPROPYL MYRISTATE; .ALPHA.-TOCOPHEROL ACETATE; CARBOMER HOMOPOLYMER, UNSPECIFIED TYPE

Germ-X 996.000/996AA
Dye Free Germ-X Advanced Hand Sanitizer with Aloe

Active ingredient

Ethyl alcohol 70%

Purpose

Antiseptic

Uses

- to decrease bacteria on the skin that could cause disease
- recommended for repeated use

Warnings

For external use only: hands

Flammable, keep away from fire or flame.

When using this product

- keep out of eyes. In case of contact with eyes, flush thoroughly with water.
- avoid contact with broken skin
- do not inhale or ingest

Stop use and ask a doctor if

- irritation and redness develop
- conditon persists for more than 72 hours

Keep out of reach of children.

If swallowed, get medical help or contact a Poison Control Center right away.

Directions

- wet hands thoroughly with product and allow to dry without wiping
- for children under 6, use only under adult supervision
- not recommended for infants

Other information

- do not store above 105⁰ F
- may discolor some fabrics
- harmful to wood finishes and plastics

Inactive ingredients

water, Aloe barbadensis leaf juice, glyceryl caprylate/caprate, glycerin, isopropyl myristate, tocopheryl acetate, carbomer, fragrance

Disclaimer

*Effective at eliminating more than 99.99% of many common harmful germs and bacteria in as little as 15 seconds.

DSP-TN-21091 DSP-MO-20087 DSP-MO-28 SDS-MO-20068

FORMULA MADE IN USA

EMPLOYEE OWNED

Adverse reaction

Dist. By Vi-Jon, LLC.

8515 Page Ave.

St. Louis, MO 63114

Pat. 9,161,982

Principal display panel

germ-x®

SINCE 1997

ADVANCED

moisturizing hand sanitizer

with Aloe & Vitamin E

Kills more than 99.99% of germs in 15 seconds*

70% ETHYL ALCOHOL

FORMULA MADE IN USA

EMPLOYEE OWNED

12 FL OZ (354 ML)